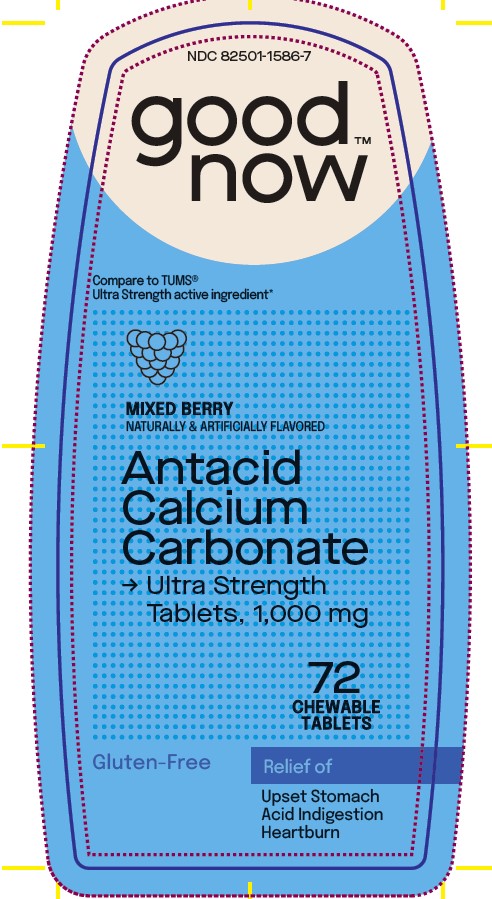 DRUG LABEL: Antacid Calcium Carbonate
NDC: 82501-1586 | Form: TABLET, CHEWABLE
Manufacturer: Gobrands, Inc
Category: otc | Type: HUMAN OTC DRUG LABEL
Date: 20241220

ACTIVE INGREDIENTS: CALCIUM CARBONATE 1000 mg/1 1
INACTIVE INGREDIENTS: ADIPIC ACID; FD&C BLUE NO. 1; FD&C RED NO. 40; MAGNESIUM STEARATE; MALTODEXTRIN; MICROCRYSTALLINE CELLULOSE; SUCROSE

Antacid Calcium Carbonate Mixed Berry

Active Ingredient (in each tablet)

Calcium Carbonate USP 1000 mg

Purpose

Antacid

Uses

relieves

• heartburn

• acid indigestion

• sour stomach

• upsetstomach associated with these symptoms

Ask a doctor or pharmacist before use if you are

presently taking a prescription drug. Antacids
may interact with certain prescription drugs.

When using this product

• do not take more than 7 tablets in 24 hours

• If pregnant do not take more than 5 tablets in 24 hours

• do not use the maximum dosage for more than 2 weeks except under the advice and supervision of a doctor

Keep out of reach of children.

Directions

adults and children 12 years of age and over: chew 2 tablets to 3 tablets as symptoms occur, or as directed by a doctor
• do not take for symptoms that persist for more than 2 weeks unless advised by a doctor

Other information

• each tablet contains: elemental calcium 400 mg
• store between 20-25° C (68-77° F)

Inactive ingredients

adipic acid, FD&C Blue No.1 , FD&C RED NO. 40, flavors, magnesium stearate, maltodextrin, microcrystalline cellulose, sugar

Principal Display Panel

NDC 82501-1586-7

good nowTM

MIXED BERRY

NATURALLY & ARTIFICIALLY FLAVORED

Antacid
Calcium
Carbonate
Ultra Strength
Tablets, 1,000 mg